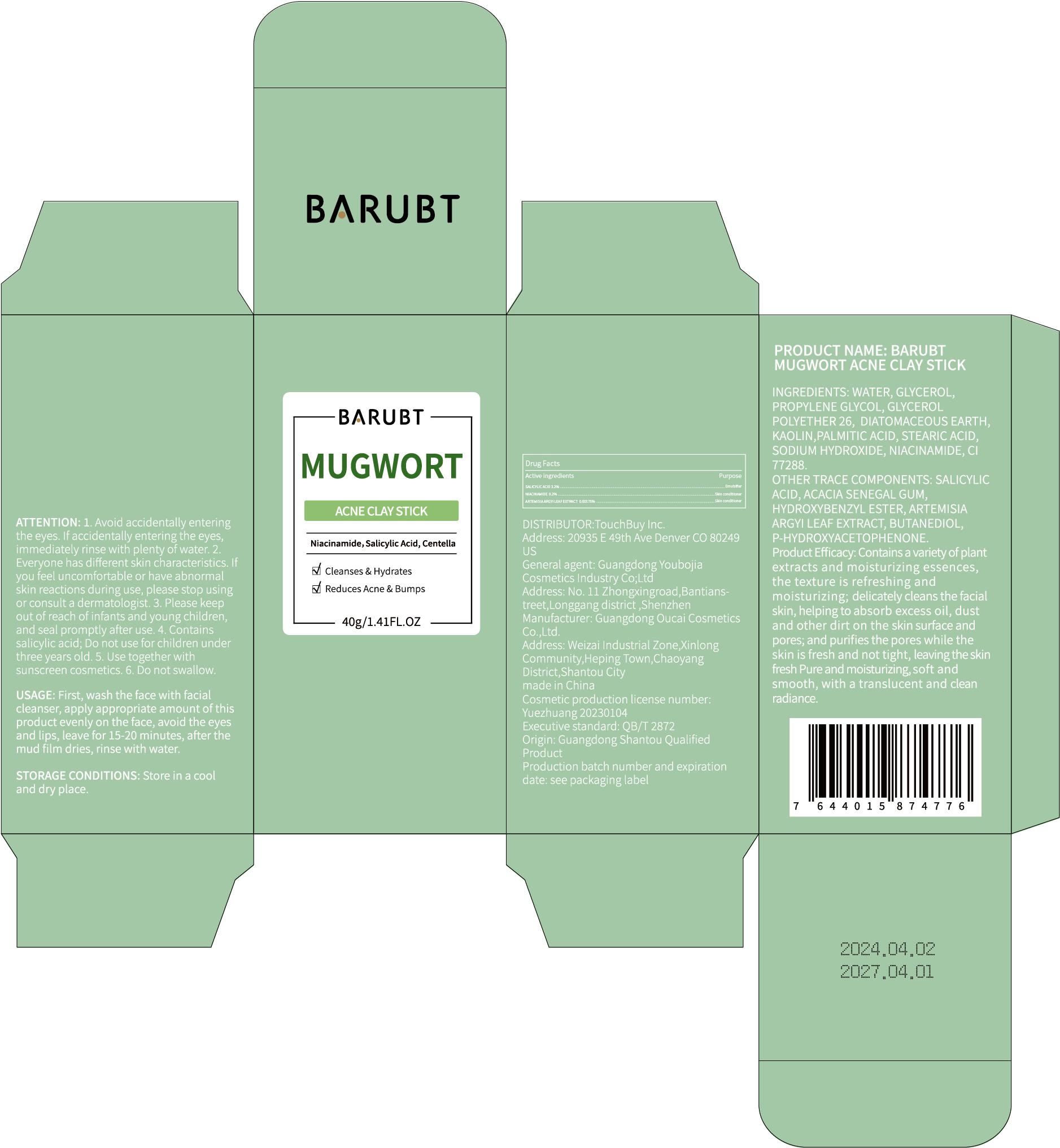 DRUG LABEL: BARUBT Mugwort Acne Clay Stick
NDC: 84712-016 | Form: PASTE
Manufacturer: Guangdong Youbaijia Cosmetic Industry Co., Ltd
Category: otc | Type: HUMAN OTC DRUG LABEL
Date: 20240917

ACTIVE INGREDIENTS: ARTEMISIA ARGYI LEAF 0.0007 g/40 g; NIACINAMIDE 0.08 g/40 g; SALICYLIC ACID 1.28 g/40 g
INACTIVE INGREDIENTS: DIATOMACEOUS EARTH 3.2 g/40 g; KAOLIN 3.2 g/40 g

ACTIVE INGREDIENT

SALICYLIC ACID 3.2%
NIACINAMIDE 0.2%
ARTEMISIA ARGYI LEAF EXTRACT 0.00175%

INACTIVE INGREDIENT

WATER
GLYCEROL
PROPYLENE GLYCOL
GLYCEROL POLYETHER 26
KAOLIN
DIATOMACEOUS EARTH
STEARIC ACID
PALMITIC ACID
SODIUM HYDROXIDE
ACACIA SEHEGAL GUM
CI 77288
BUTANEDIOL
HYDROXYBENZYL ESTER
P-HYDROXYACETOPHENONE

Do not use on damaged skin.

Keep away from children. Do not swallow.

PURPOSE

moisturizing, delicately cleans the facial skin

QUESTIONS

Contact name: Jessie Peng
Company phone number: +1 818 579 7288
Company e-mail: jessie@registeragentllc.com

STOP USE

lf you feel uncomfortable or have abnormal skin reactions during use, please stop using or consult a dermatologist

WHEN USING

Avoid accidentally enteringthe eyes. lf accidentally entering the eyes,immediately rinse with plenty of water

WARNINGS

For external use only.

STORAGE AND HANDLING

Keep away from light and in a dry place.

INDICATIONS AND USAGE

Product Efficacy: contains a variety of plant extracts and moisturizing essences,the texture is refreshing and moisturizing; delicately cleans the facial skin, helping to absorb excess oil, dust and other dirt on the skin surface and pores, and purifies the pores while the skin is fresh and not tight, leaving the skin fresh Pure and moisturizing, soft and smooth, with a translucent and clean radiance.

DOSAGE AND ADMINISTRATION

USAGE: First, wash the face with facial cleanser, apply appropriate amount of this product evenly on the face, avoid the eyes and lips, leave for 15-20 minutes, after the mud film dries, rinse with water.